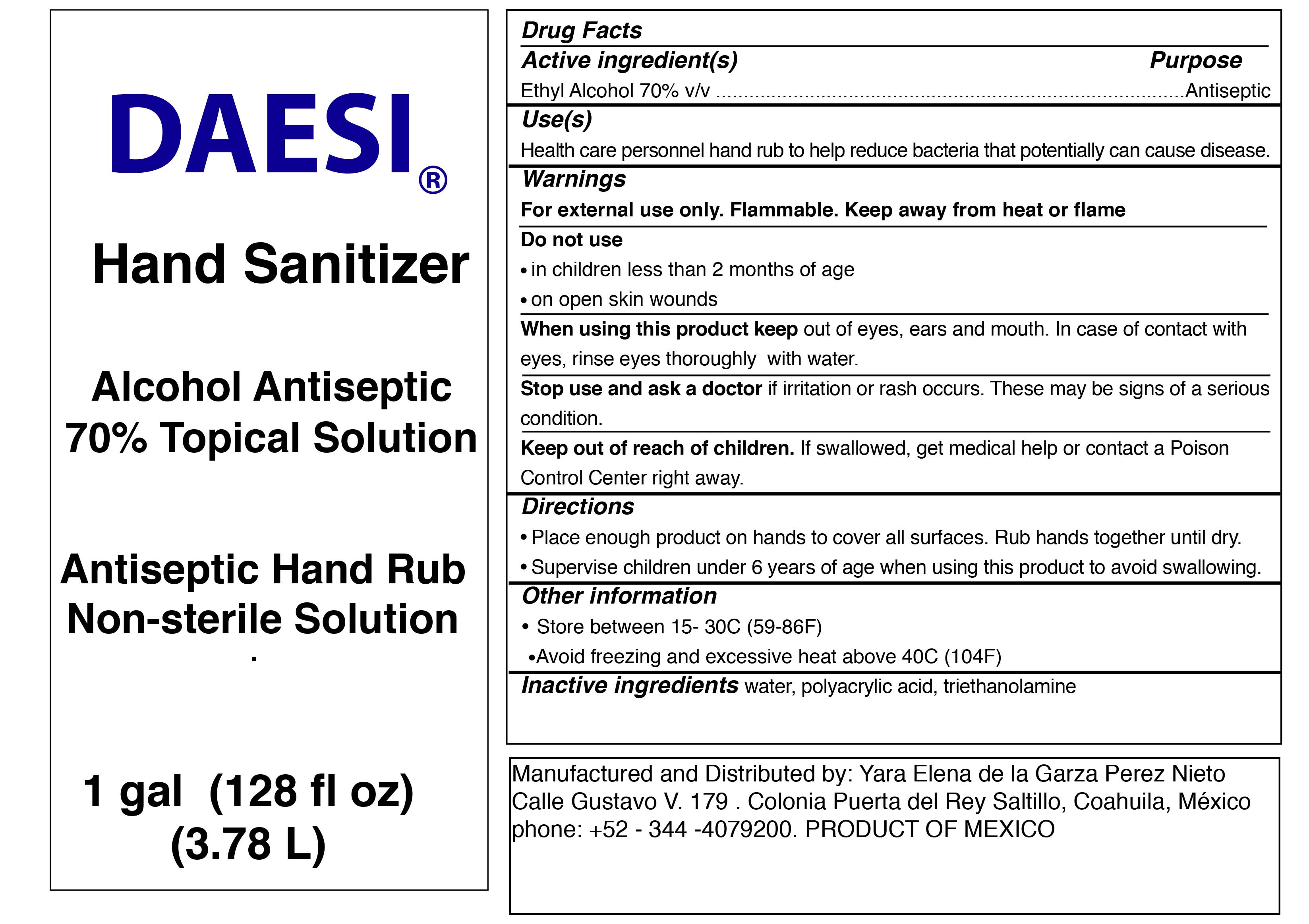 DRUG LABEL: DAESI
NDC: 77268-001 | Form: GEL
Manufacturer: YARA ELENA DE LA GARZA PEREZ NIETO
Category: otc | Type: HUMAN OTC DRUG LABEL
Date: 20200504

ACTIVE INGREDIENTS: ALCOHOL 70 mL/100 mL
INACTIVE INGREDIENTS: WATER 29.4 mL/100 mL; POLYACRYLIC ACID (8000 MW) 0.3 mL/100 mL; TROLAMINE 0.3 mL/100 mL

Directions

Place enough product on hands to cover all surfaces. Rub hands together until dry.

Supervise children under 6 years of age when using this product to avoid swallowing.

Warnings

Flammable, keep away from fire and flames

For external use only.

Inactive ingredients

water, polyacrylic acid, and triethanolamine.

Use(s)

Health care personnel hand rub to help reduce bacteria that potentially can cause disease.

Keep out of reach of children

If swallowed, get medical help or contact a Poison Control Center right away.

Purpose

Antiseptic

Active Ingredient(s)

Ethyl alcohol 70% v/v

Do not use

In children less than 2 months of age
On open skin wounds

PACKAGE LABEL

3.78 L NDC: 77268-001-01